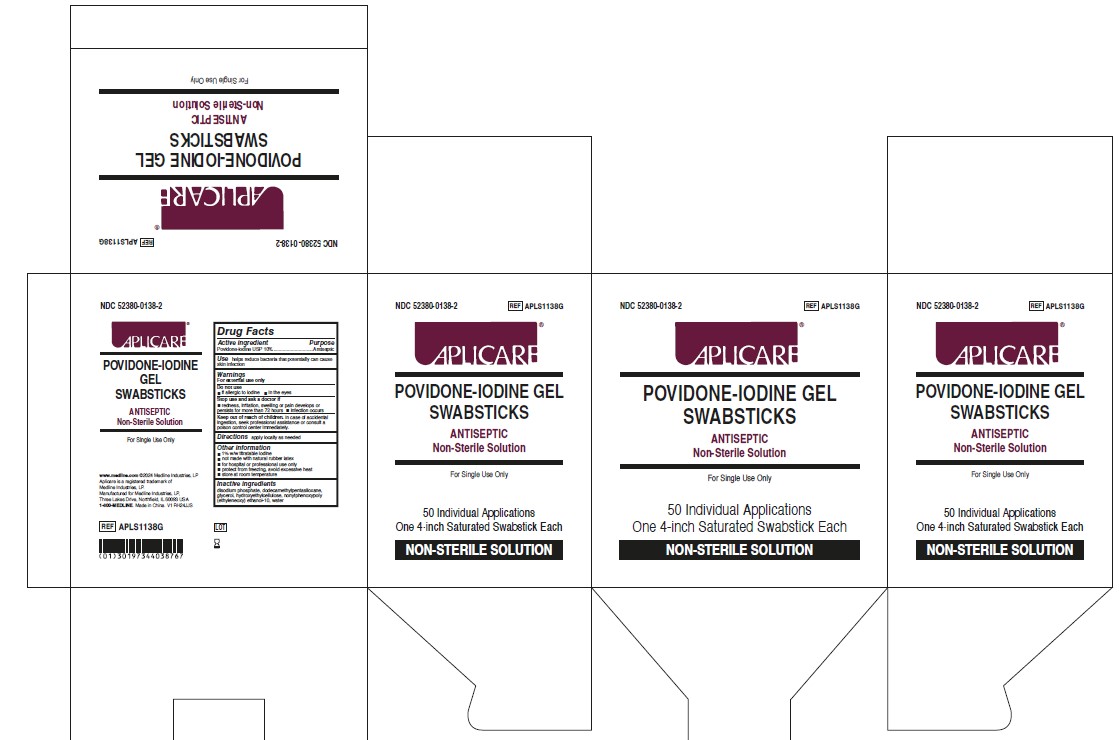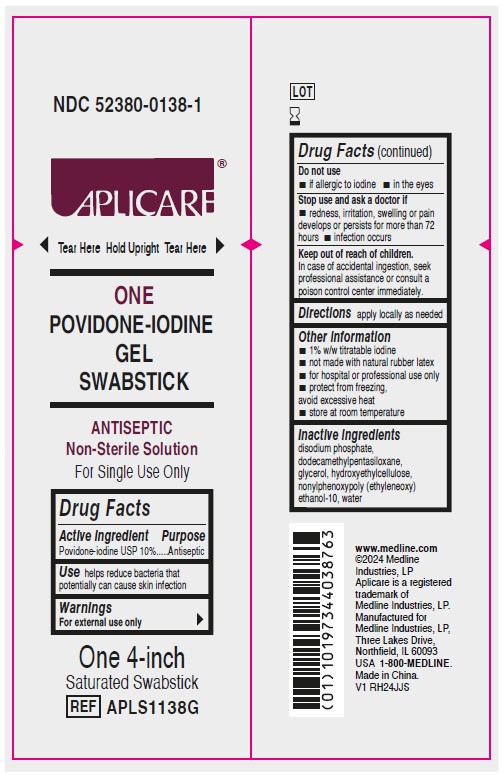 DRUG LABEL: Aplicare
NDC: 52380-0138 | Form: SWAB
Manufacturer: Aplicare Products LLC
Category: otc | Type: HUMAN OTC DRUG LABEL
Date: 20251218

ACTIVE INGREDIENTS: POVIDONE-IODINE 10 mg/1 mL
INACTIVE INGREDIENTS: DODECAMETHYLPENTASILOXANE; SODIUM PHOSPHATE, DIBASIC, ANHYDROUS; HYDROXYETHYL CELLULOSE, UNSPECIFIED; WATER; NONOXYNOL-2; GLYCERIN

0138 Aplicare PVP-I Gel Swabstick

Active ingredient

Povidone-iodine USP 10%

Purpose

Antiseptic

Use

helps reduce bacteria that potentially can cause skin infection

Warnings

For external use only

Do not use

- if allergic to iodine
- in the eyes

Stop use and ask a doctor if

- redness, irritation, swelling or pain develops or persists for more than 72 hours
- infection occurs

Keep out of reach of children.

In case of accidental ingestion, seek professional assistance or consult a poison control center immediately.

Directions

apply locally as needed

Other information

- 1% w/w titratable iodine
- not made with natural rubber latex
- for hospital or professional use only
- protect from freezing, avoid excessive heat
- store at room temperature

Inactive ingredients

disodium phosphate, dodecamethylpentasiloxane, glycerol, hydroxyethylcellulose, nonylphenoxypoly (ethyleneoxy) ethanol-10, water

Manufacturing information

www.medline.com

©2024 Medline Industries, LP

Aplicare is a registered trademark of Medline Industries, LP.

Manufactured for Medline Industries, LP, Three Lakes Drive, Northfield, IL 60093 USA

1-800-MEDLINE.

Made in China.